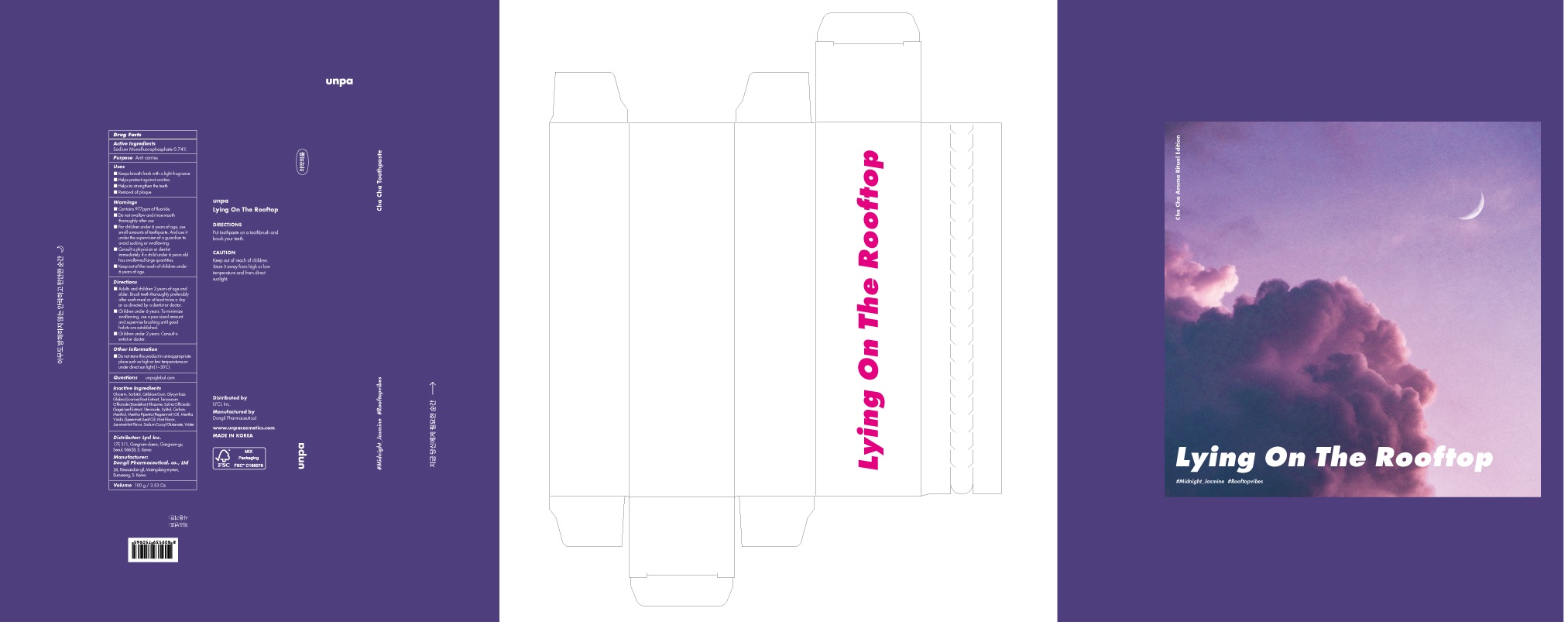 DRUG LABEL: unpa cha cha toothpaste Jasmine Mint
NDC: 73134-090 | Form: PASTE, DENTIFRICE
Manufacturer: Lycl Inc.
Category: otc | Type: HUMAN OTC DRUG LABEL
Date: 20210923

ACTIVE INGREDIENTS: Sodium Monofluorophosphate 0.74 g/100 g
INACTIVE INGREDIENTS: WATER; Glycerin; Sorbitol

ACTIVE INGREDIENT

Sodium Monofluorophosphate 0.74%

INACTIVE INGREDIENTS

Glycerin, Sorbitol, Cellulose Gum, Glycyrrhiza Glabra (Licorice) Root Extract, Taraxacum Officinale (Dandelion) Rhizome, Salvia Officinalis (Sage) Leaf Extract, Stevioside, Xylitol, Carbon, Menthol, Mentha Piperita (Peppermint) Oil, Mentha Viridis (Spearmint) Leaf Oil, Mint Flavor, JasmineMint Flavor, Sodium Cocoyl Glutamate, Water

PURPOSE

Anti carries

WARNINGS

■ Contains 977ppm of fluoride.
■ Do not swallow and rinse mouth thoroughly after use
■ For children under 6 years of age, use small amounts of toothpaste. And use it under the supervision of a guardian to avoid sucking or swallowing.
■ Consult a physician or dentist immediately if a child under 6 years old has swallowed large quantities.
■ Keep out of the reach of children under 6 years of age.

KEEP OUT OF REACH OF CHILDREN

■ Keep out of the reach of children under 6 years of age.

Uses

■ Keeps breath fresh with a light fragrance
■ Helps protect against cavities
■ Helps to strengthen the teeth
■ Removal of plaque

Directions

■ Adults and children 2 years of age and older: Brush teeth thoroughly preferably after each meal or at least twice a day or as directed by a dentist or doctor.
■ Children under 6 years: To minimize swallowing, use a pea-sized amount and supervise brushing until good habits are established.
■ Children under 2 years: Consult a dentist or doctor.

Other Information

■ Do not store this product in an inappropriate place such as high or low temperatures or under direct sun light (1~30℃)

QUESTIONS

■ unpaglobal.com